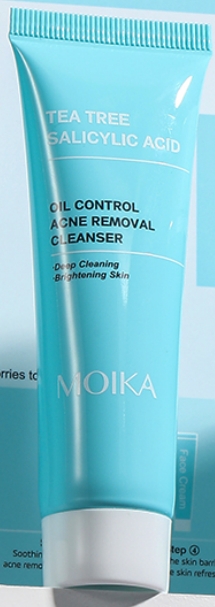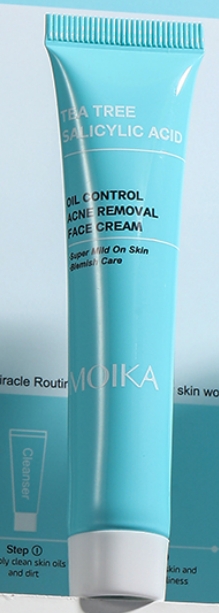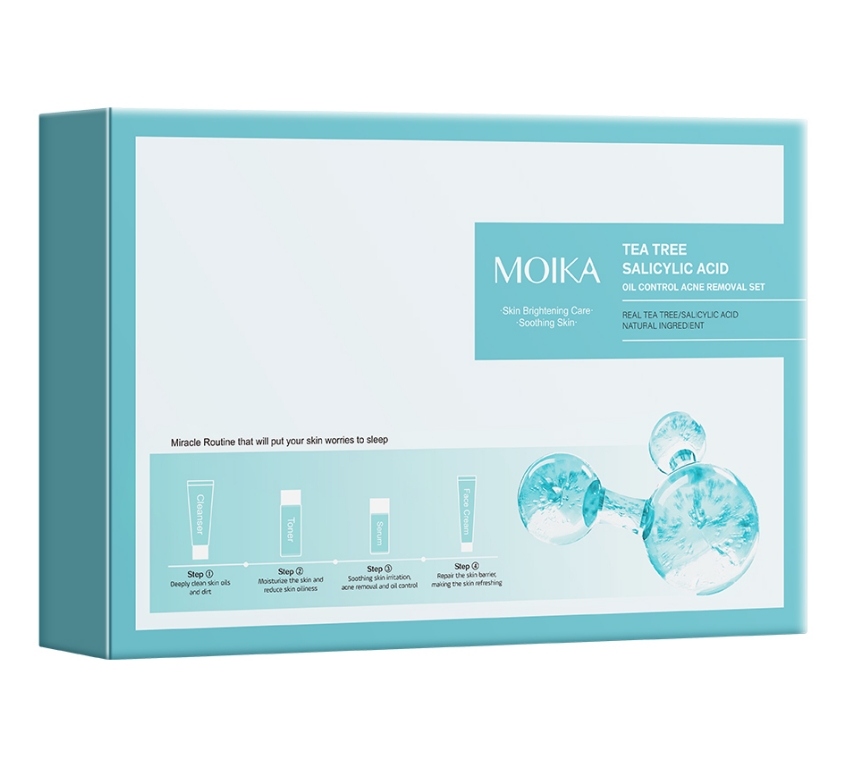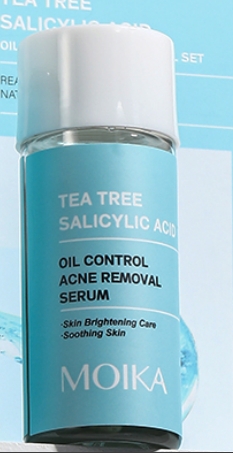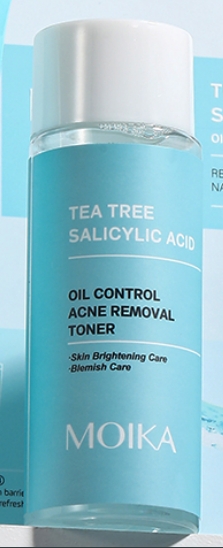 DRUG LABEL: TREE SALICYLIC ACID ACNE REMOVAL
NDC: 84507-042 | Form: LIQUID
Manufacturer: Guangdong Miaolian Cosmetics Co., Ltd.
Category: otc | Type: HUMAN OTC DRUG LABEL
Date: 20250626

ACTIVE INGREDIENTS: SALICYLIC ACID 0.001 mg/100 mL
INACTIVE INGREDIENTS: GLYCERIN; SODIUM SALICYLATE; PHENOXYETHANOL; EDETATE DISODIUM; PEG-40 HYDROGENATED CASTOR OIL; FRAGRANCE FRESH CITRUS FLORAL ORC1501495; SORBITOL; PEG-10; XANTHAN GUM; WATER; MALTITOL; MELALEUCA ALTERNIFOLIA (TEA TREE) LEAF OIL; MANNITOL; ALLANTOIN; DIAZOLIDINYL UREA; METHYLPARABEN

DOSAGE AND ADMINISTRATION

• clean the skin thoroughly before applying this product
• cover the entire affected area with a thin layer one to three times daily

• because excessive drying of the skin may occur, start with one application daily, then gradually increase to two or three times daily if needed or as directed by a doctor
• if bothersome dryness or peeling occurs, reduce application to once a day or every other day
• if going outside, apply sunscreen after using this product. If irritation or sensitivity develops, stop use of both products and ask a doctor.

WARNINGS

For external use only

When using this product

skin irritation and dryness is more likely to occur if you use another topical acne medication at the same time. If irritation occurs, only use one topical acne medication at a time.

Keep out of reach of children.

If swallowed, get medical help or contact a Poison Control Center immediately.

INACTIVE INGREDIENT

WATER
SODIUM LAURETH SULFA
COCAMIDOPROPYL BETAINE
SODIUM CHLORID
DECYL GLUCOSIDE
COCAMIDE MEA
PHENOXYETHANOL
SODIUM LAUROYL SARCOSINATE
STYRENE/ACRYLATES COPOLYMER
DISODIUM EDTA
METHYLPARABEN
ACRYLATES/C10-30 ALKYL ACRYLATE
CROSSPOLYMER
POLYQUATERNIUM-7
GLYCERIN
FRAGRANCE
SODIUM HYDROXIDE
ETHYLHEXYLGLYCERIN
HAMAMELIS VIRGINIANA (WITCH HAZEL) WATER
BIFIDA FERMENT FILTRATE
MELALEUCA ALTERNIFOLIA (TEA
TREE) LEAF OIL
ETHANOLAMINE
GLYCERYL CAPRYLAT
ORYZA SATIVA (RICE) LEES WATER
SODIUM CARBONATE
LACTOBACILLUS/RICE FERMENT
ALGAE OLIGOSACCHARIDES
SODIUM PCA
SODIUM LACTATE
1,2-HEXANEDIOL
PENTYLENE GLYCOL
ARGININ
YEAST EXTRACT
ASPARTIC ACID
HYDROXYACETOPHENONE
PCA
GLYCINE
ALANINE
CHONDRUS CRISPUS EXTRACT
SERINE
VALINE
PROLINE
THREONINE
ISOLEUCINE
SOLUBLE COLLAGEN
HISTIDINE
PHENYLALANINE

ACTIVE INGREDIENT

SALICYLIC ACID--------0.24%

PURPOSE

Treats acne - Helps prevent the development of new acne blemishes

INDICATIONS AND USAGE

• use every morning and evening
• apply a dime-size amount to damp skin and gently massage, avoiding the eye area
• rinse well
• if bothersome dryness or peeling occurs, reduce application use
• may be used on chest or back

Keep out of reach of children.

If swallowed, get medical help or contact a Poison Control Center right away.